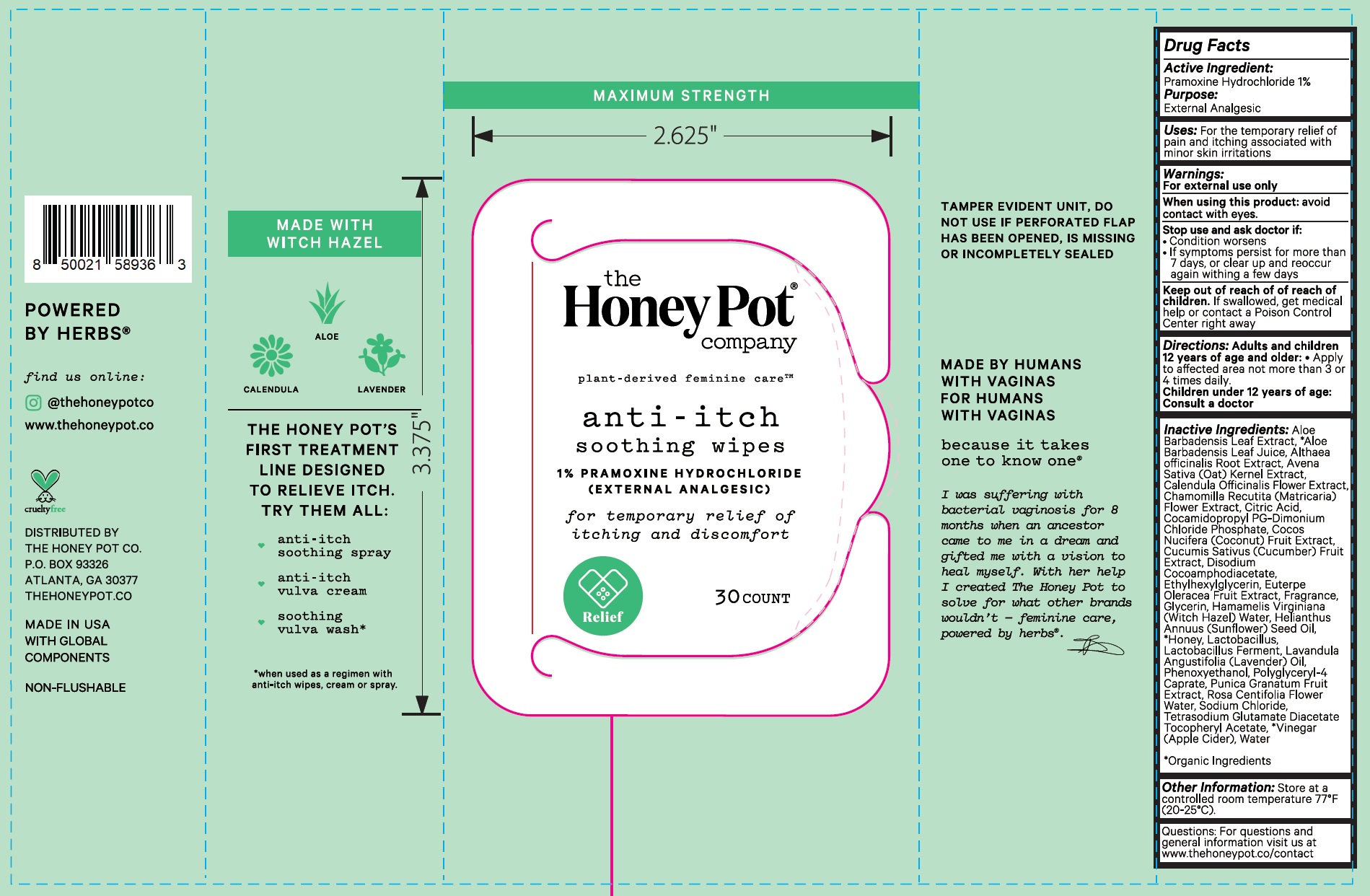 DRUG LABEL: Anti-Itch Soothing Wipes 1 Pramoxine Hydrochloride
NDC: 82637-9363 | Form: CLOTH
Manufacturer: The Honey Pot Company LLC
Category: otc | Type: HUMAN OTC DRUG LABEL
Date: 20251216

ACTIVE INGREDIENTS: PRAMOXINE HYDROCHLORIDE 10 mg/1 mL
INACTIVE INGREDIENTS: CALENDULA OFFICINALIS FLOWER; ALOE VERA LEAF; ALTHAEA OFFICINALIS ROOT; OAT; CHAMOMILE; CITRIC ACID MONOHYDRATE; COCAMIDOPROPYL PROPYLENE GLYCOL-DIMONIUM CHLORIDE PHOSPHATE; COCONUT; CUCUMBER; DISODIUM COCOAMPHODIACETATE; ETHYLHEXYLGLYCERIN; ACAI; GLYCERIN; HAMAMELIS VIRGINIANA TOP WATER; SUNFLOWER OIL; HONEY; LAVENDER OIL; PHENOXYETHANOL; POLYGLYCERYL-4 CAPRATE; POMEGRANATE; ROSA CENTIFOLIA FLOWER OIL; SODIUM CHLORIDE; TETRASODIUM GLUTAMATE DIACETATE; .ALPHA.-TOCOPHEROL ACETATE; ACETIC ACID; WATER

Anti-Itch Soothing Wipes 1 % Pramoxine Hydrochloride

Active Ingredient:

Pramoxine Hydrochloride 1%

Purpose:

External Analgesic

Uses:

For the temporary relief of pain and itching associated with minor skin irritations

Warnings:

For external use only

When using this product:

avoid contact with eyes.

Stop use and ask doctor if:

- Condition worsens
- If symptoms persist for more than 7 days, or clear up and reoccur again withing a few days

Keep out of reach of of reach of children.

If swallowed, get medical help or contact a Poison Control Center right away

Directions:

Adults and children 12 years of age and older:

Children under 12 years of age: Consult a doctor

- Apply to affected area not more than 3 or 4 times daily.

Inactive Ingredients:

Aloe Barbadensis Leaf Extract, *Aloe Barbadensis Leaf Juice, Althaea officinalis Root Extract, Avena Sativa (Oat) Kernel Extract, Calendula Officinalis Flower Extract, Chamomilla Recutita (Matricaria) Flower Extract, Citric Acid, Cocamidopropyl PG-Dimonium Chloride Phosphate, Cocos Nucifera (Coconut) Fruit Extract, Cucumis Sativus (Cucumber) Fruit Extract, Disodium Cocoamphodiacetate, Ethylhexylglycerin, Euterpe Oleracea Fruit Extract, Fragrance, Glycerin, Hamamelis Virginiana (Witch Hazel) Water, Helianthus Annuus (Sunflower) Seed Oil, *Honey, Lactobacillus, Lactobacillus Ferment, Lavandula Angustifolia (Lavender) Oil, Phenoxyethanol, Polyglyceryl-4 Caprate, Punica Granatum Fruit Extract, Rosa Centifolia Flower Water, Sodium Chloride, Tetrasodium Glutamate Diacetate Tocopheryl Acetate, *Vinegar (Apple Cider), Water *Organic Ingredients

Other Information:

Store at a controlled room temperature 77°F (20-25°C).

Questions:

For questions and general information visit us at www.thehoneypot.co/contact